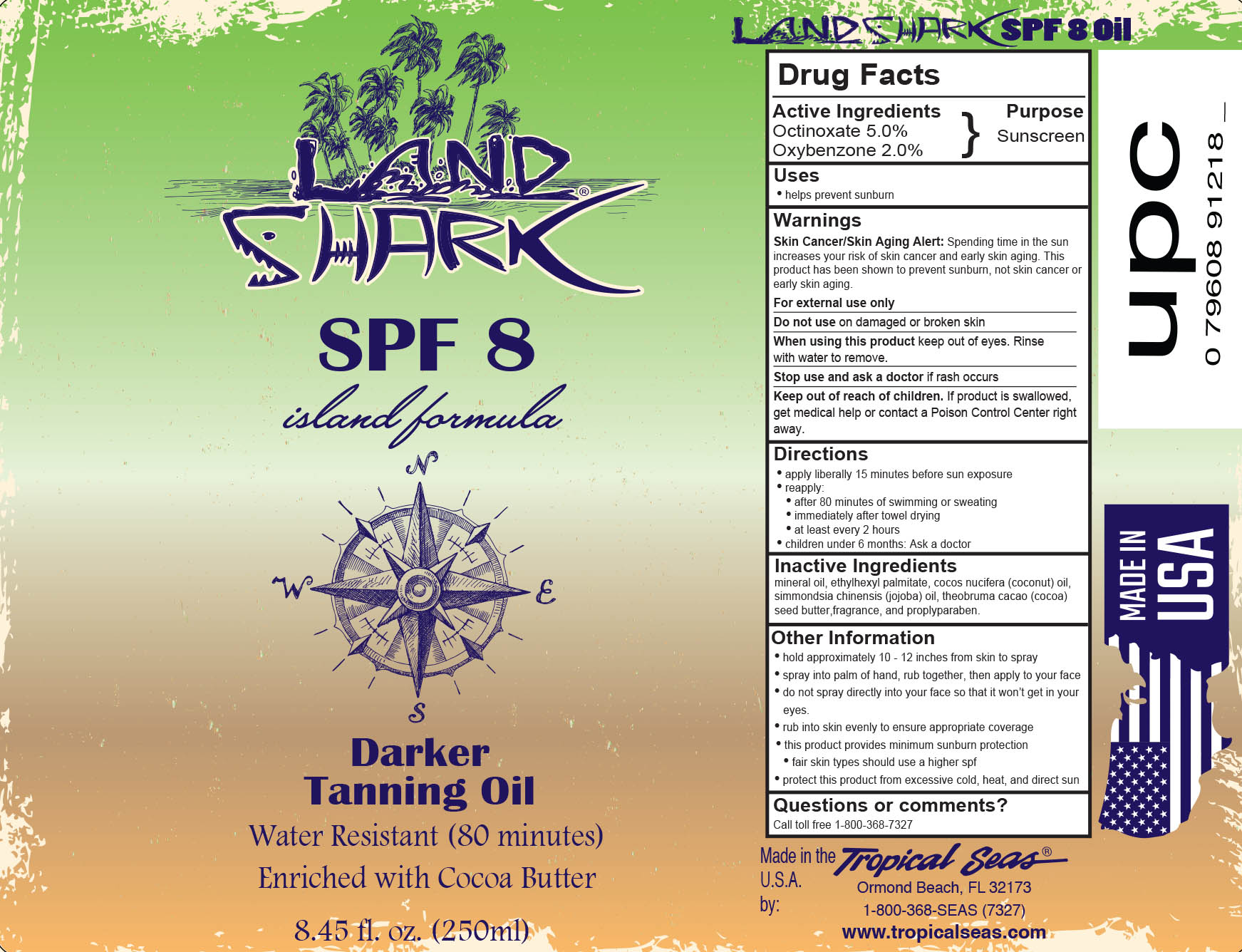 DRUG LABEL: Land Shark SPF 8
NDC: 52854-928 | Form: OIL
Manufacturer: Tropical Seas, Inc.
Category: otc | Type: HUMAN OTC DRUG LABEL
Date: 20251104

ACTIVE INGREDIENTS: OCTINOXATE 5 g/100 mL; OXYBENZONE 2 g/100 mL
INACTIVE INGREDIENTS: MINERAL OIL; ETHYLHEXYL PALMITATE; COCONUT OIL; JOJOBA OIL; PROPYLPARABEN; COCOA BUTTER

Drug Facts

Active Ingredients

Octinoxate 5.0%

Oxybenzone 2.0%

Purpose

Sunscreen

Uses

- helps prevent sunburn

Warnings

Skin Cancer/Skin Aging Alert: Spending time in the sun increases your risk of skin cancer and early skin aging. This product has been shown to prevent sunburn, not skin cancer or early skin aging.

For external use only

Do not use on damaged or broken skin

When using this product keep out of eyes. Rinse with water to remove.

Stop use and ask a doctor if rash occurs

Keep out of reach of children. If product is swallowed, get medical help or contact a Poison Control Center right away.

Directions

- apply liberally 15 minutes before sun exposure
- reapply:
  - after 80 minutes of swimming or sweating
  - immediately after towel drying
  - at least every 2 hours
- children under 6 months: Ask a doctor

Inactive Ingredients

mineral oil, ethylhexyl palmitate, cocos nucifera (coconut) oil, simmondsia chinensis (jojoba) oil, theobroma cacao (cocoa) seed butter, fragrance, and propylparaben.

Other Information

- hold apprximately 10 - 12 inches from skin to spray
- spray into palm of hand, rub together, then apply to your face
- do not spray directly into your face so that it won't get in your eyes.
- rub into skin evenly to ensure appropriate coverage
- this product provides minimum sunburn protection
- fair skin types should use a higher spf
- protect this product from excessive cold, heat, and direct sun

Questions or comments?

Call toll free 1-800-368-7327

Principal Display Panel - Bottle Label

250 ml NDC: 52854-928-01